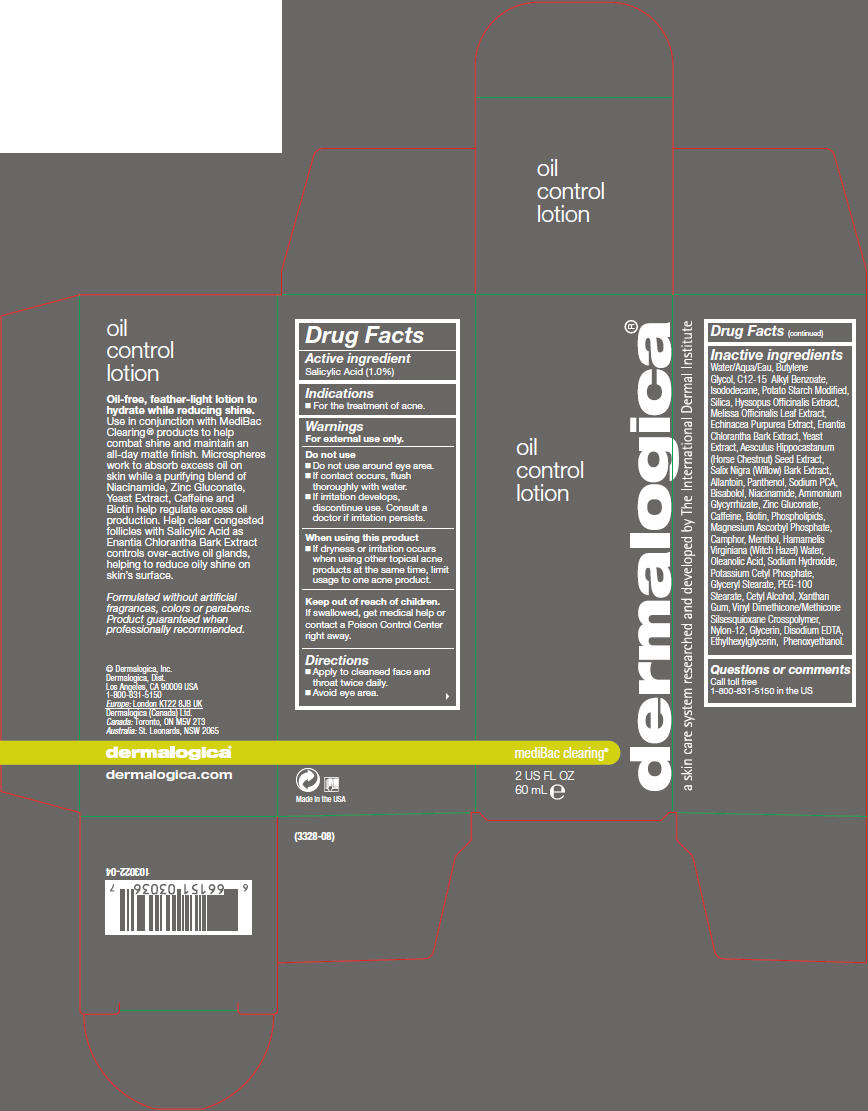 DRUG LABEL: Oil Control
NDC: 68479-808 | Form: LOTION
Manufacturer: Dermalogica, Inc.
Category: otc | Type: HUMAN OTC DRUG LABEL
Date: 20151120

ACTIVE INGREDIENTS: Salicylic Acid 10 mg/1 mL
INACTIVE INGREDIENTS: Water; Butylene Glycol; Alkyl (C12-15) Benzoate; Isododecane; Silicon Dioxide; Hyssopus Officinalis Flowering Top; Melissa Officinalis Leaf; Echinacea Purpurea; Annickia Chlorantha Bark; Yeast, Unspecified; Horse Chestnut; Allantoin; Panthenol; Glycerin; Sodium Pyrrolidone Carboxylate; Levomenol; Omega-3 Fatty Acids; Niacinamide; Ammonium Glycyrrhizate; Zinc Gluconate; Caffeine; Biotin; Oleanolic Acid; Salix Nigra Bark; Magnesium Ascorbyl Phosphate; Hamamelis Virginiana Top Water; Potassium Cetyl Phosphate; Glyceryl Monostearate; PEG-100 Stearate; Cetyl Alcohol; Xanthan Gum; Nylon-12; Camphor (Synthetic); Menthol, Unspecified Form; Sodium Hydroxide; Edetate Disodium; Ethylhexylglycerin; Phenoxyethanol

Oil Control Lotion

Drug Facts

Active ingredient

Salicylic Acid (1.0%)

Indications

PURPOSE

- For the treatment of acne.

Warnings

For external use only.

Do not use

- Do not use around eye area.
- If contact occurs, flush thoroughly with water.
- If irritation develops, discontinue use. Consult a doctor if irritation persists.

When using this product

- If dryness or irritation occurs when using other topical acne products at the same time, limit usage to one acne product.

Keep out of reach of children. If swallowed, get medical help or contact a Poison Control Center right away.

Directions

- Apply to cleansed face and throat twice daily.
- Avoid eye area.

Inactive ingredients

Water/Aqua/Eau, Butylene Glycol, C12-15 Alkyl Benzoate, Isododecane, Potato Starch Modified, Silica, Hyssopus Officinalis Extract, Melissa Officinalis Leaf Extract, Echinacea Purpurea Extract, Enantia Chlorantha Bark Extract, Yeast Extract, Aesculus Hippocastanum (Horse Chestnut) Seed Extract, Salix Nigra (Willow) Bark Extract, Allantoin, Panthenol, Sodium PCA, Bisabolol, Niacinamide, Ammonium Glycyrrhizate, Zinc Gluconate, Caffeine, Biotin, Phospholipids, Magnesium Ascorbyl Phosphate, Camphor, Menthol, Hamamelis Virginiana (Witch Hazel) Water, Oleanolic Acid, Sodium Hydroxide, Potassium Cetyl Phosphate, Glyceryl Stearate, PEG-100 Stearate, Cetyl Alcohol, Xanthan Gum, Vinyl Dimethicone/Methicone Silsesquioxane Crosspolymer, Nylon-12, Glycerin, Disodium EDTA, Ethylhexylglycerin, Phenoxyethanol.

Questions or comments

Call toll free
1-800-831-5150 in the US

PRINCIPAL DISPLAY PANEL - 60 mL Bottle Carton

oil
control
lotion

dermalogica®

mediBac clearing®

2 US FL OZ
60 mL e